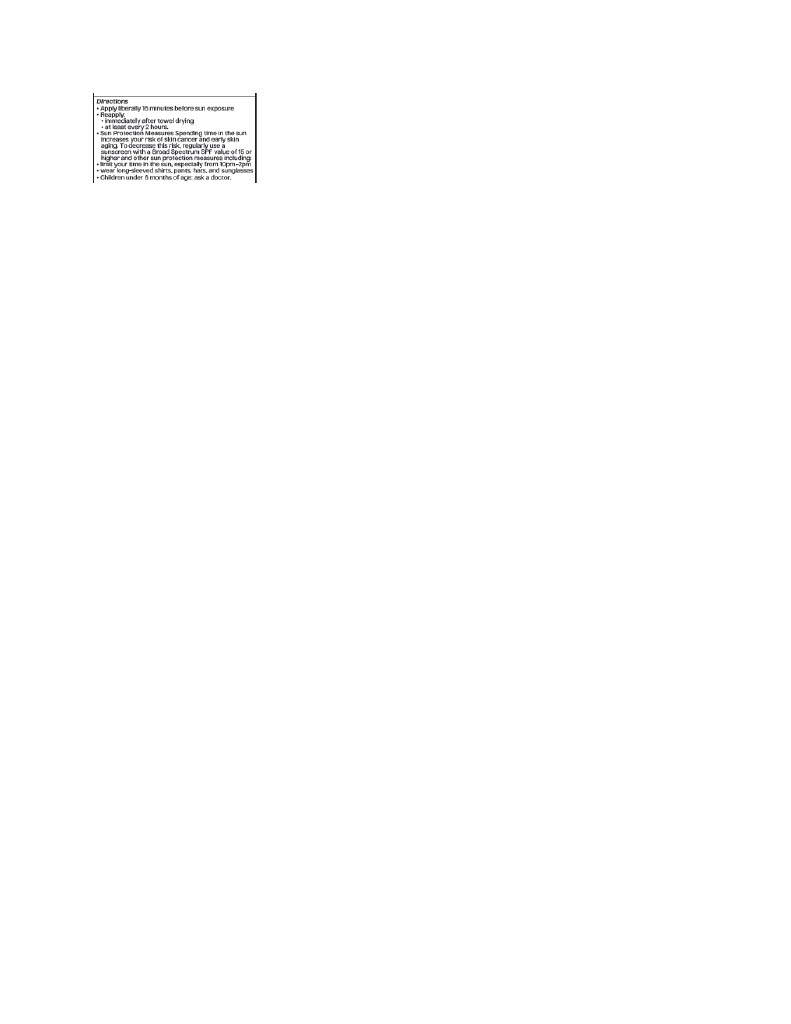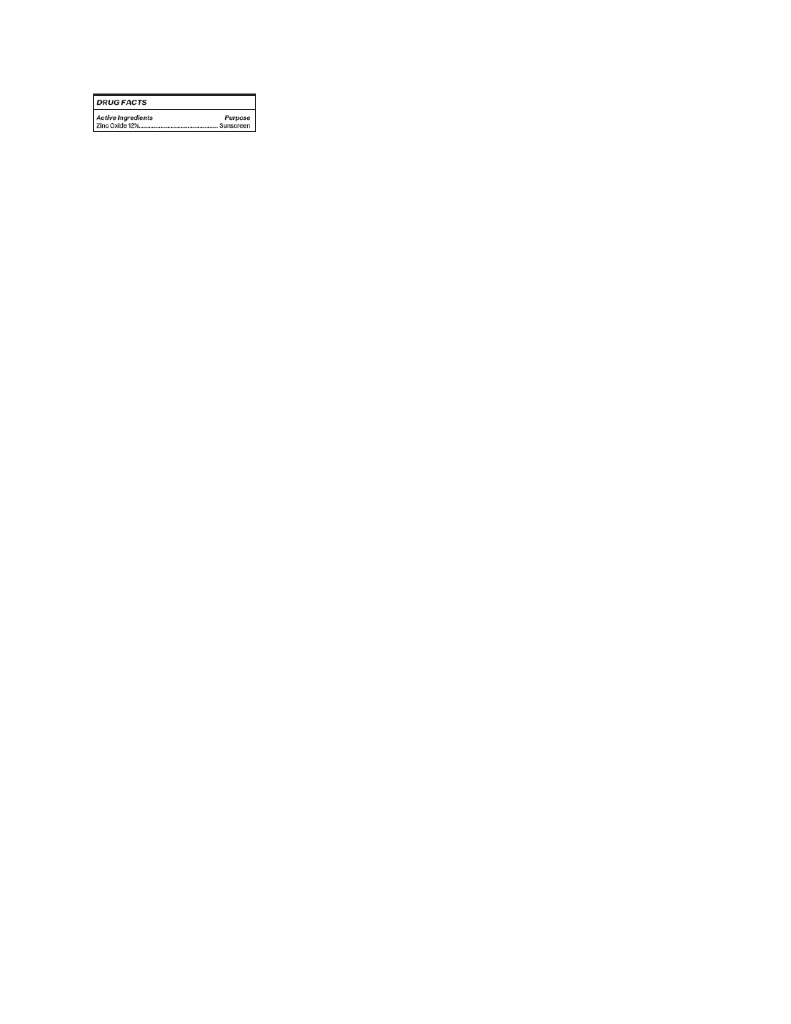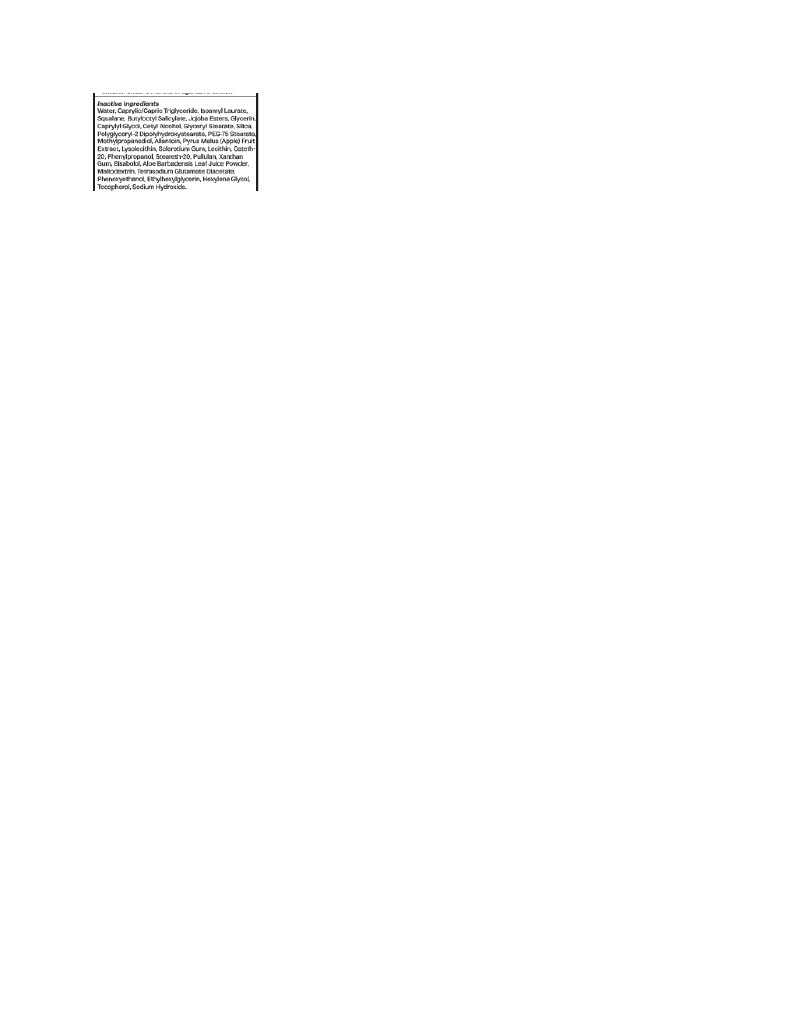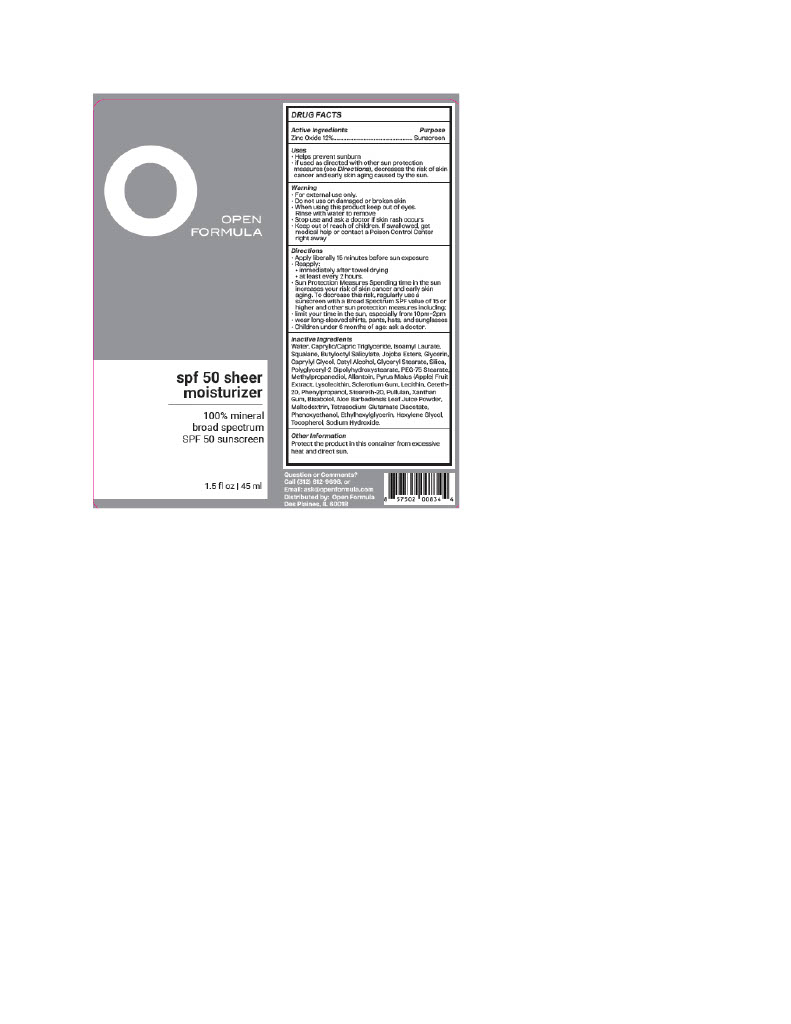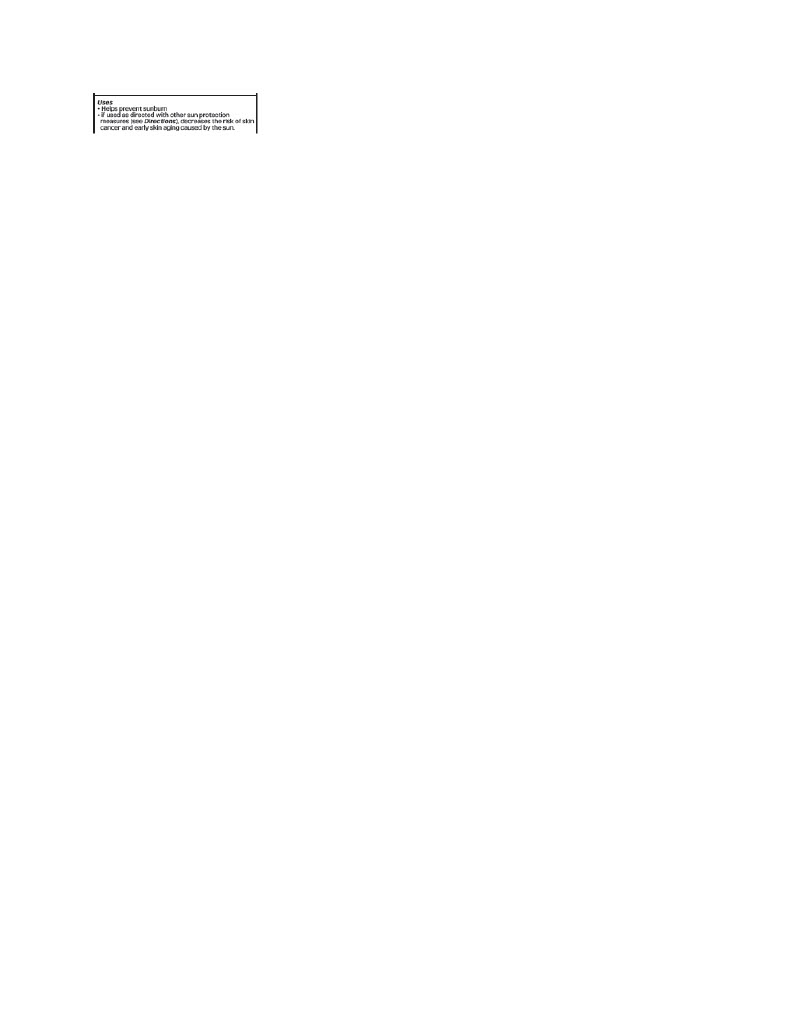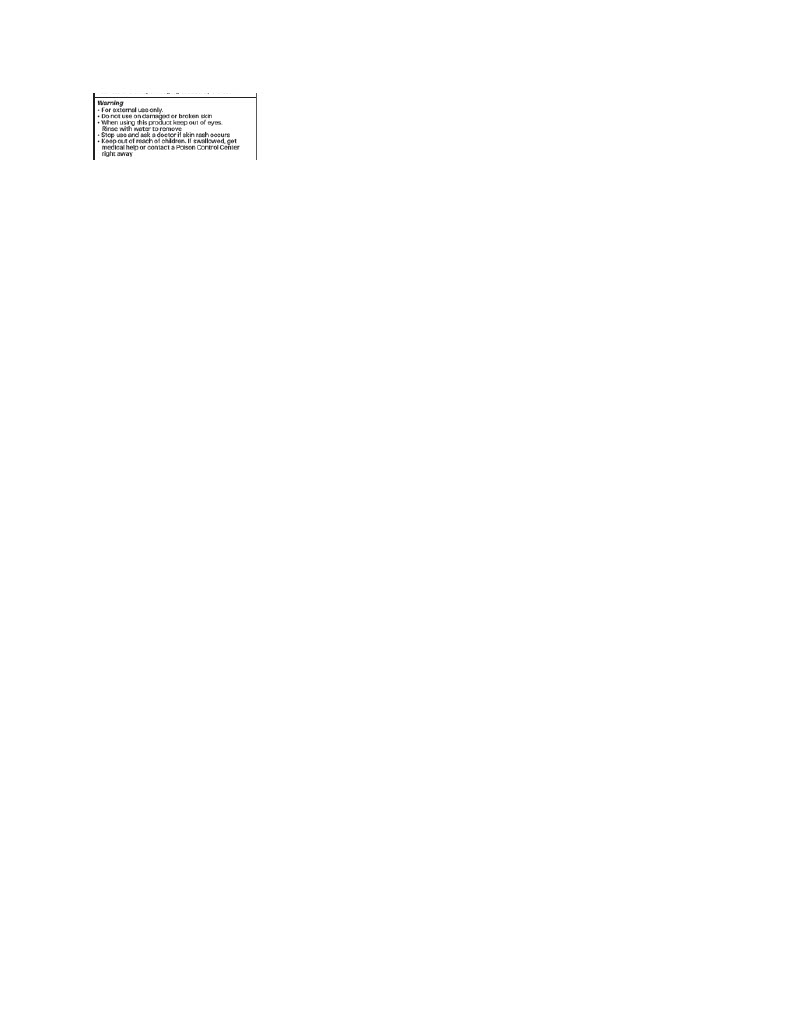 DRUG LABEL: Organys Open Formula Sheer
NDC: 83612-1391 | Form: LOTION
Manufacturer: Organys Beauty
Category: otc | Type: HUMAN OTC DRUG LABEL
Date: 20251009

ACTIVE INGREDIENTS: ZINC OXIDE 132 mg/1 mL
INACTIVE INGREDIENTS: BUTYLOCTYL SALICYLATE; CETETH-20; PULLULAN; LECITHIN, SOYBEAN; POLYGLYCERYL-2 DIPOLYHYDROXYSTEARATE; PHENYLPROPANOL; HYDROLYZED JOJOBA ESTERS (ACID FORM); METHYLPROPANEDIOL; CAPRYLYL GLYCOL; XANTHAN GUM; ISOAMYL LAURATE; HEXYLENE GLYCOL; TOCOPHEROL; CETYL ALCOHOL; ETHYLHEXYLGLYCERIN; GLYCERIN; SILICON DIOXIDE; WATER; .ALPHA.-BISABOLOL, (+)-; SQUALANE; CYCLODEXTRINS; STEARETH-20

Organys Open Formula Sheer